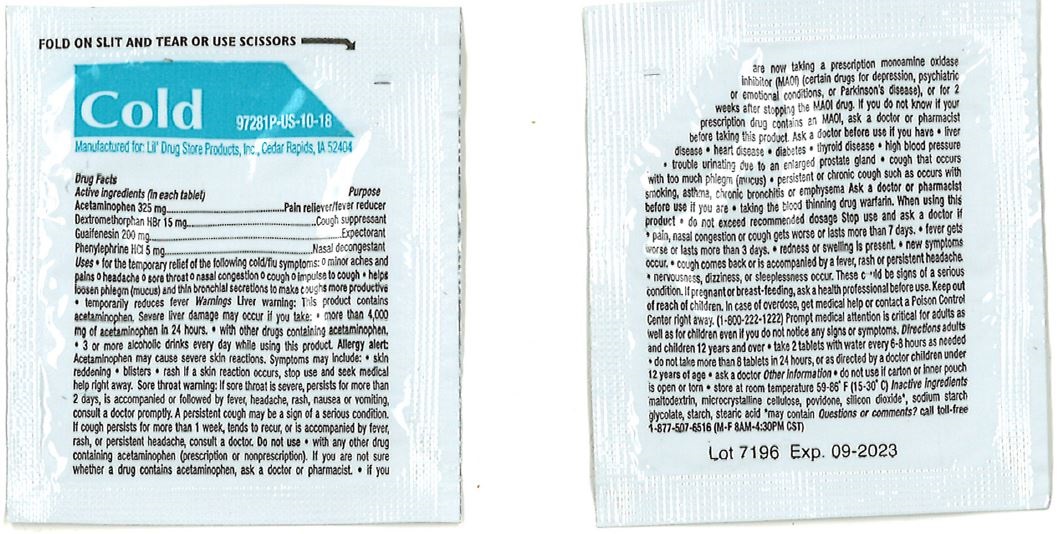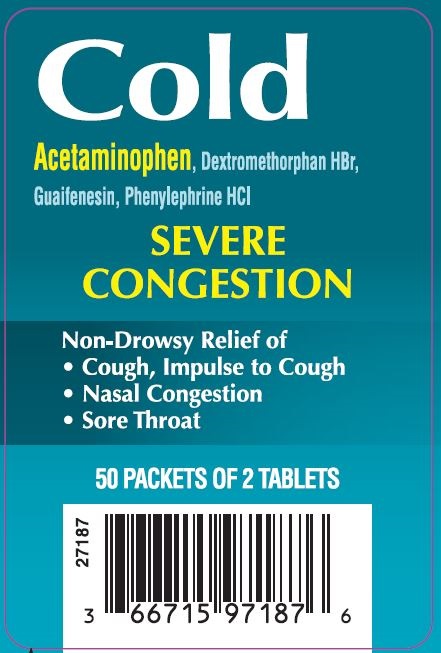 DRUG LABEL: Cold Severe Congestion
NDC: 66715-9818 | Form: TABLET
Manufacturer: Lil' Drug Store Products, Inc.
Category: otc | Type: HUMAN OTC DRUG LABEL
Date: 20220809

ACTIVE INGREDIENTS: PHENYLEPHRINE HYDROCHLORIDE 5 mg/1 1; DEXTROMETHORPHAN HYDROBROMIDE 15 mg/1 1; ACETAMINOPHEN 325 mg/1 1; GUAIFENESIN 200 mg/1 1
INACTIVE INGREDIENTS: SODIUM STARCH GLYCOLATE TYPE A CORN; SILICON DIOXIDE; MALTODEXTRIN; STARCH, CORN; STEARIC ACID; CELLULOSE, MICROCRYSTALLINE; POVIDONE, UNSPECIFIED

Cold Severe Congestion

Drug Facts

Active ingredients

Active ingredients (in each tablet)
Acetaminophen 325 mg

Dextromethorphan HBr 15 mg
Guaifenesin 200 mg
Phenylephrine HCI 5 mg

Purpose

Pain reliever/fever reducer
Cough suppressant
Expectorant
Nasal decongestant

Uses

■ for the temporary relief of the following cold/flu symptoms:
■ minor aches and pains

■ headache

■ sore throat
■ nasal congestion

■ cough

■ impulse to cough
■ helps loosen phlegm (mucus) and thin bronchial secretions to make coughs more productive
■ temporarily reduces fever

Warnings

Liver warning

Liver warning: This product contains acetaminophen. Severe liver damage
may occur if you take:

■ more than 4,000 mg of acetaminophen in 24 hours
■ with other drugs containing acetaminophen
■ 3 or more alcoholic drinks every day while using this product.

Allergy alert

Allergy alert: Acetaminophen may cause severe skin reactions. Symptoms may include:

■ skin reddening

■ blisters

■ rash

If a skin reaction occurs, stop use and seek medical help right away.

Sore throat warning: If sore throat is severe, persists for more than 2 days, is accompanied or followed by fever, headache, rash, nausea or vomiting, consult a doctor promptly.
A persistent cough may be a sign of a serious condition. If cough persists for more than 1 week, tends to recur, or is accompanied by fever, rash, or persistent headache, consult a doctor.

Do not use

■ with any other drug containing acetaminophen (prescription or nonprescription). If you are not sure whether a drug contains acetaminophen, ask a doctor or pharmacist.
■ if you are now taking a prescription monoamine oxidase inhibitor (MAOI) (certain drugs for depression, psychiatric or emotional conditions, or Parkinson’s disease), or for 2 weeks after stopping the MAOI drug. If you do not know if your prescription drug contains an MAOI, ask a doctor or pharmacist before taking this product.

Ask a doctor before use if you have

■ liver disease

■ heart disease
■ diabetes

■ thyroid disease

■ high blood pressure
■ trouble urinating due to an enlarged prostate gland
■ cough that occurs with too much phlegm (mucus)
■ persistent or chronic cough such as occurs with smoking, asthma, chronic bronchitis or emphysema

Ask a doctor or pharmacist before use if you are

■ taking the blood thinning drug warfarin

When using this product

■ do not exceed recommended dosage

Stop use and ask a doctor if

■ pain, nasal congestion or cough gets worse or lasts more than 7 days
■ fever gets worse or lasts more than 3 days
■ redness or swelling is present
■ new symptoms occur
■ cough comes back or is accompanied by a fever, rash or persistent headache
■ nervousness, dizziness, or sleeplessness occur.
These could be signs of a serious condition.

If pregnant or breast-feeding, ask a health professional before use.

Keep out of reach of children. In case of overdose, get medical help or contact a Poison Control Center right away. (1-800-222-1222) Prompt medical attention is critical for adults as well as for children even if you do not notice any signs or symptoms.

Directions

adults and children; 12 years and over | ■ take 2 tablets with water every 6-8 hours as needed; ■ do not take more than 8 tablets in 24 hours, or as directed by a doctor
children under; 12 years of age | ask a doctor

Other information

■ store at room temperature 59-86˚ F (15-30˚ C)

Inactive ingredients

maltodextrin, microcrystalline cellulose, povidone, silicon dioxide*, sodium starch glycolate, starch, stearic acid
*may contain

Questions or comments?

call toll-free 1-877-507-6516 (M-F 8AM-4:30PM CST)

PDP/Package

Cold

Acetaminophen, Dextromethorphan HBr,

Guaifenesin, Phenylephrine HCl

SEVERE

CONGESTION

Non-Drowsy Relief of

- Cough, Im[pulse to Cough
- Nasal Congestion
- Sore Throat
- 50 PACKETS OF 2 TABLETS

[barcode]

3 66715 97187 6